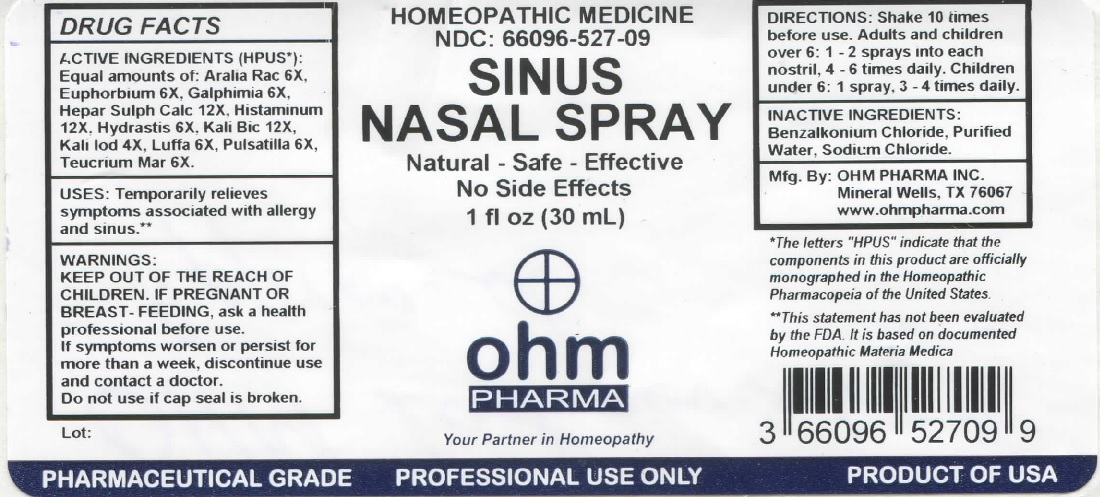 DRUG LABEL: OHM Sinus Nasal
NDC: 66096-527 | Form: SPRAY
Manufacturer: OHM PHARMA INC.
Category: homeopathic | Type: HUMAN OTC DRUG LABEL
Date: 20211229

ACTIVE INGREDIENTS: ARALIA RACEMOSA ROOT 6 [hp_X]/30 mL; EUPHORBIA RESINIFERA RESIN 6 [hp_X]/30 mL; GALPHIMIA GLAUCA FLOWERING TOP 6 [hp_X]/30 mL; CALCIUM SULFIDE 12 [hp_X]/30 mL; HISTAMINE DIHYDROCHLORIDE 12 [hp_X]/30 mL; GOLDENSEAL 12 [hp_X]/30 mL; POTASSIUM DICHROMATE 12 [hp_X]/30 mL; POTASSIUM IODIDE 4 [hp_X]/30 mL; LUFFA OPERCULATA FRUIT 6 [hp_X]/30 mL; ANEMONE PULSATILLA 6 [hp_X]/30 mL; TEUCRIUM MARUM 6 [hp_X]/30 mL
INACTIVE INGREDIENTS: BENZALKONIUM CHLORIDE; WATER; SODIUM CHLORIDE

OHM Sinus Nasal Spray

ACTIVE INGREDIENT

ACTIVE INGREDIENTS (HPUS*): Equal amounts of: Aralia Rac 6X, Euphorbium 6X, Galphimia 6X, Hepar Sulph Calc 12X, Histaminum 12X, Hydrastis 6X, Kali Bic 12X, Kali Iod 4X, Luffa 6X, Pulsatilla 6X, Teucrium Mar 6X.

*The letters "HPUS" indicate that the components in this product are officially monographed in the Homeopathic Pharmacopeia of the United States.

INDICATIONS AND USAGE

USES: Temporarily relieves symptoms associated with allergy and sinus.**

**This statement has not been evaluated by the FDA. It is based on documented Homeopathic Materia Medica.

WARNINGS

WARNINGS: IF PREGNANT OR BREAST-FEEDING, ask a health professional before use. If symptoms worsen or persist for more than a week, discontinue use and contact a doctor.

- KEEP OUT OF REACH OF CHILDREN.

DOSAGE AND ADMINISTRATION

DIRECTIONS: Shake 10 times before use. Adults and children over 6: 1-2 sprays into each nostril, 4-6 times daily. Children under 6: 1 spray, 3-4 times daily.

Do not use if cap seal is broken.

INACTIVE INGREDIENT

INACTIVE INGREDIENTS: Benzalkonium Chloride, Purified Water, Sodium Chloride.

QUESTIONS

Mfg. By: OHM PHARMA INC. Mineral Wells, TX 76067

www.ohmpharma.com

PACKAGE LABEL

HOMEOPATHIC MEDICINE

NDC: 66096-527-09

SINUS NASAL SPRAY

Natural - Safe - Effective

No Side Effects

1 fl oz (30 mL)

PRODUCT OF USA

PURPOSE

Allergy / Sinus relief.